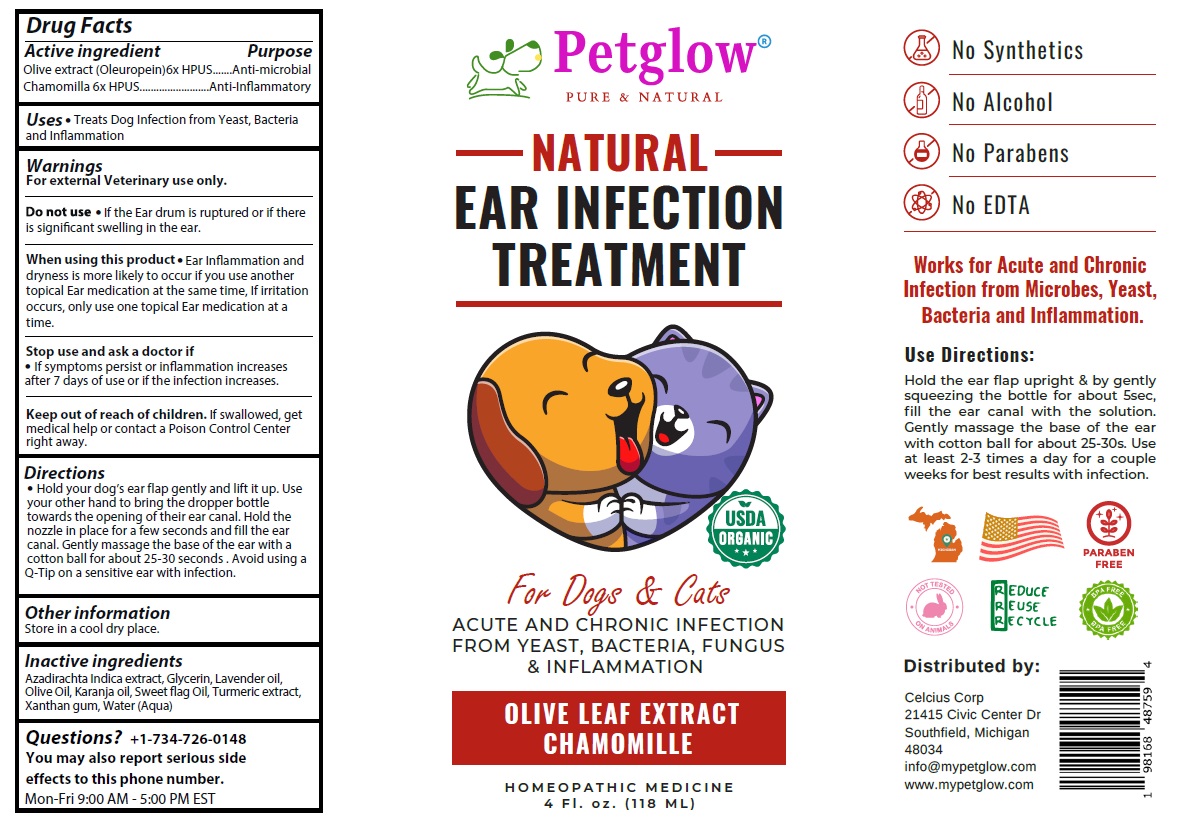 DRUG LABEL: Petglow NATURAL EAR INFECTION TREATMENT
NDC: 83819-300 | Form: SOLUTION
Manufacturer: Celcius Corp.
Category: homeopathic | Type: OTC ANIMAL DRUG LABEL
Date: 20260216

ACTIVE INGREDIENTS: OLEA EUROPAEA (OLIVE) LEAF POWDER 6 [hp_X]/118 mL; CHAMOMILE 6 [hp_X]/118 mL
INACTIVE INGREDIENTS: AZADIRACHTA INDICA SEED OIL; GLYCERIN; LAVENDER OIL; OLIVE OIL; KARUM SEED OIL; CALAMUS OIL; TURMERIC; XANTHAN GUM; WATER

Petglow® NATURAL EAR INFECTION TREATMENT

Active ingredient

Olive extract (Oleuropein) 6x HPUS
Chamomilla 6x HPUS

Purpose

Anti-microbial
Anti-Inflammatory

Uses

• Treats Dog Infection from Yeast, Bacteria and Inflammation

Warnings

For external Veterinary use only.

Do not use • If the Ear drum is ruptured or if there is significant swelling in the ear.

When using this product • Ear Inflammation and dryness is more likely to occur if you use another topical Ear medication at the same time, If irritation occurs, only use one topical Ear medication at a time.

Stop use and ask a doctor if
• If symptoms persist or inflammation increases after 7 days of use or if the infection increases.

Keep out of reach of children. If swallowed, get medical help or contact a Poison Control Center right away.

Directions

• Hold your dog’s ear flap gently and lift it up. Use your other hand to bring the dropper bottle towards the opening of their ear canal. Hold the nozzle in place for a few seconds and fill the ear canal. Gently massage the base of the ear with a cotton ball for about 25-30 seconds . Avoid using a Q-Tip on a sensitive ear with infection.

Other information

Store in a cool dry place.

Inactive ingredients

Azadirachta Indica extract, Glycerin, Lavender oil, Olive Oil, Karanja oil, Sweet flag Oil, Turmeric extract, Xanthan gum, Water (Aqua)

Questions?

+1-734-726-0148
You may also report serious side effects to this phone number.
Mon-Fri 9:00 AM - 5:00 PM EST

PURE & NATURAL

USDA ORGANIC

For Dogs & Cats

ACUTE AND CHRONIC INFECTION FROM YEAST, BACTERIA, FUNGUS & INFLAMMATION

HOMEOPATHIC MEDICINE

No Synthetics
No Alcohol
No Parabens
No EDTA

Works for Acute and Chronic Infection from Microbes, Yeast, Bacteria and Inflammation.

NOT TESTED ON ANIMALS

REDUCE
REUSE
RECYCLE

BPA FREE

Distributed by:

Celcius Corp
21415 Civic Center Dr
Southfield, Michigan
48034
info@mypetglow.com
www.mypetglow.com